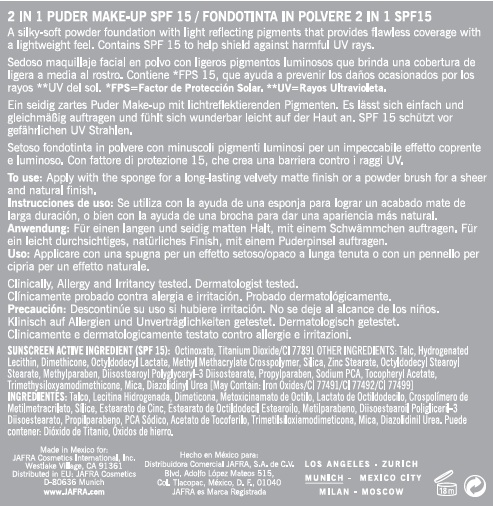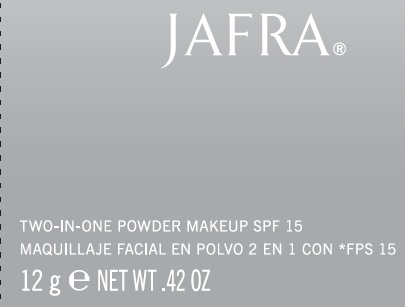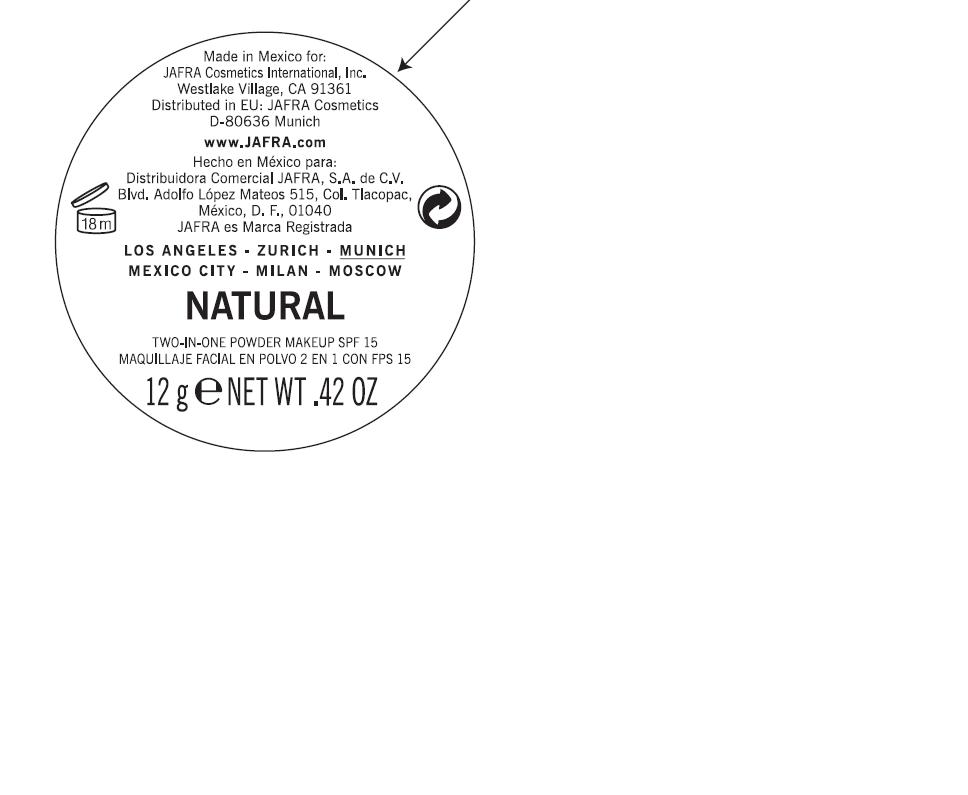 DRUG LABEL: 2 IN 1 POWDER MAKE-UP
NDC: 68828-057 | Form: POWDER
Manufacturer: JAFRA COSMETICS INTERNATIONAL
Category: otc | Type: HUMAN OTC DRUG LABEL
Date: 20120511

ACTIVE INGREDIENTS: OCTINOXATE 5 g/100 g; TITANIUM DIOXIDE 3.25 g/100 g
INACTIVE INGREDIENTS: TALC; HYDROGENATED SOYBEAN LECITHIN; DIMETHICONE; OCTYLDODECYL LACTATE; METHYL METHACRYLATE; SILICON DIOXIDE; ZINC STEARATE; OCTYLDODECYL STEAROYL STEARATE; METHYLPARABEN; POLYGLYCERYL-3 DIISOSTEARATE; PROPYLPARABEN; TRIMETHYLSILOXYSILICATE (M/Q 0.66); MICA; DIAZOLIDINYL UREA; SODIUM PYRROLIDONE CARBOXYLATE; ALPHA-TOCOPHEROL ACETATE; FERRIC OXIDE RED; FERRIC OXIDE YELLOW; FERROSOFERRIC OXIDE

2-IN-1 POWDER MAKE-UP SPF-15

SUNSCREEN ACTIVE INGREDIENT (SPF 15):
OCTINOXATE, TITANIUM DIOXIDE/CI77891

PURPOSE: SUNSCREEN

INACTIVE INGREDIENT

OTHER INGREDIENTS: TALC, HYDROGENATED LECITHIN, DIMETHICONE, OCTYLDODECYL LACTATE, METHYL METHACRYLATE CROSSPOLYMER, SILICA, ZINC STEARATE, OCTYLDODECYL STEAROYL STEARATE, METHYLPARABEN, DIISOSTEAROYL POLYGLYCERYL-3 DIISOSTEARATE, PROPYLPARABEN, SODIUM PCA, TOCOPHERYL ACETATE, TRIMETHYLSILOXYAMODIMETHICONE, MICA, DIAZOLIDINYL UREA [MAY CONTAIN, +/-: IRON OXIDES/CI 77491/CI 77492/CI 77499]

INDICATIONS AND USAGE

CONTAINS SPF 15 TO HELP SHIELD AGAINST HARMFUL UV RAYS.

DOSAGE AND ADMINISTRATION

TO USE: APPLY WITH THE SPONGE FOR A LONG-LASTING VELVETY MATTE FINISH OR A POWDER BRUSH FOR A SHEER AND NATURAL FINISH.

WARNINGS

DISCONTINUE USE IF IRRITATION OCCURS.

KEEP OUT OF REACH OF CHILDREN.

PACKAGE LABEL

JAFRA

TWO-IN-ONE POWDER MAKEUP SPF 15